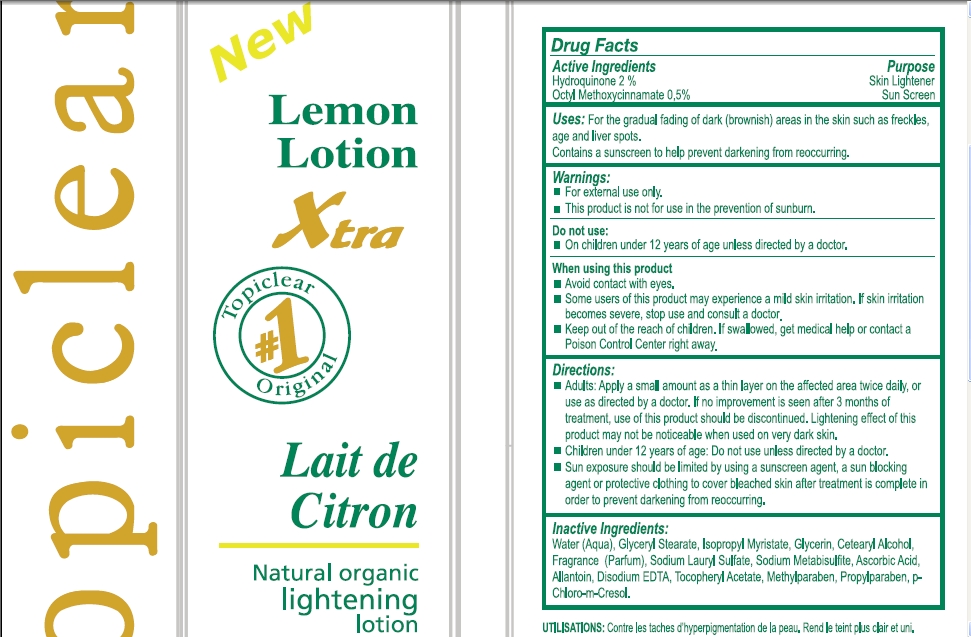 DRUG LABEL: Topiclear Xtra lemon beauty
NDC: 66129-031 | Form: LOTION
Manufacturer: International Beauty Exchange 
Category: otc | Type: HUMAN OTC DRUG LABEL
Date: 20110602

ACTIVE INGREDIENTS: HYDROQUINONE 10 mL/500 mL; OCTINOXATE 2.5 mL/500 mL
INACTIVE INGREDIENTS: WATER; GLYCERYL STEARATE CITRATE; CETOSTEARYL ALCOHOL; GLYCERIN; ISOPROPYL MYRISTATE; ALLANTOIN; ASCORBIC ACID; SODIUM METABISULFITE; .ALPHA.-TOCOPHEROL ACETATE, D-; SODIUM LAURYL SULFATE; EDETATE DISODIUM; METHYLPARABEN; PROPYLPARABEN; CHLOROCRESOL

Drug Facts

ACTIVE INGREDIENT

Hydroquinone 2%

Ethylhexyl Methoxycinnamate (Octyl Methoxycinnamate) 0.5%

WARNINGS

For external use only

DO NOT USE

On children under 12 years of age unless directed by a doctor

WHEN USING

Avoid contact with eyes.

PURPOSE

Skin Lightener